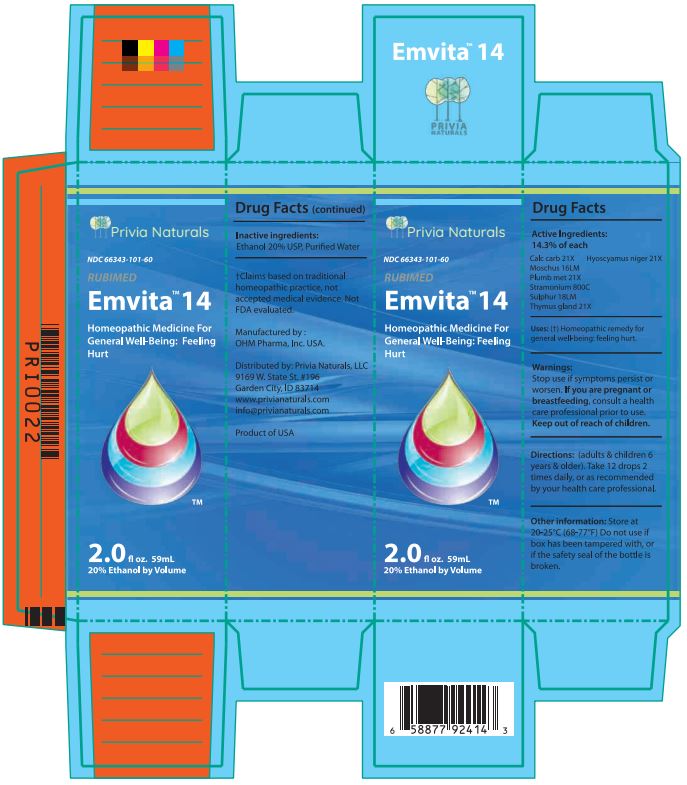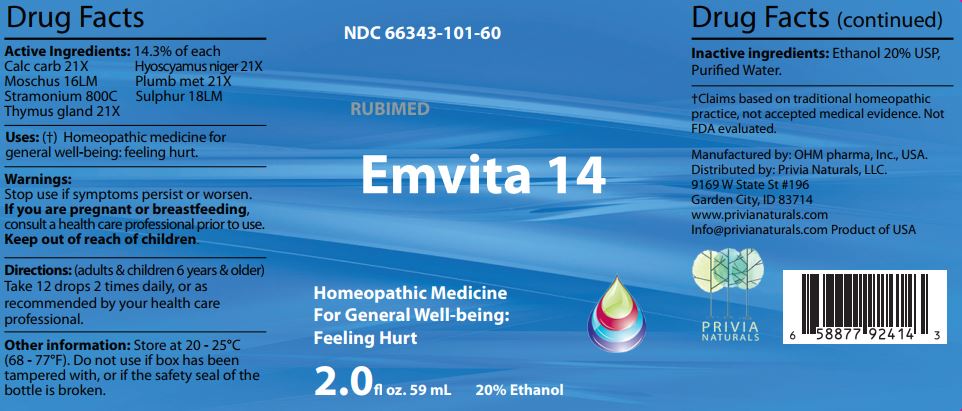 DRUG LABEL: Emvita 14
NDC: 66343-101 | Form: LIQUID
Manufacturer: RUBIMED AG
Category: homeopathic | Type: HUMAN OTC DRUG LABEL
Date: 20241029

ACTIVE INGREDIENTS: OYSTER SHELL CALCIUM CARBONATE, CRUDE 21 [hp_X]/60 mL; HYOSCYAMUS NIGER 21 [hp_X]/60 mL; MOSCHUS MOSCHIFERUS MUSK SAC RESIN 16 [hp_M]/60 mL; LEAD 21 [hp_X]/60 mL; DATURA STRAMONIUM 800 [hp_C]/60 mL; SULFUR 18 [hp_M]/60 mL; BOS TAURUS THYMUS 21 [hp_X]/60 mL
INACTIVE INGREDIENTS: ALCOHOL; WATER

Emvita 14

ACTIVE INGREDIENT

Drug Facts Active Ingredients: (HPUS*) 14.3% of each

Calc carb 21X Hyoscyamus niger 21X
Moschus 16LM Plumb met 21X
Stramonium 800C Sulphur 18LM
Thymus gland 21X

*The letters "HPUS" indicate that the components in this product are officially monographed in the Homeopathic Pharmacopoeia of the United States. †Claims based on traditional homeopathic practice, not accepted medical evidence. Not FDA evaluated.

INDICATIONS AND USAGE

Uses: (†) Homeopathic remedy for general well being: feeling hurt.

Warnings:

Stop use if symptoms persist or worsen.

If you are pregnant or breastfeeding,consult a healthcare professional prior to use.

Keep out of reach of children.

DOSAGE AND ADMINISTRATION

Directions: (adults & children 6 years & older)

Take 12 drops 2 times daily, or as recommended by your health care professional.

Other information: Store at 20 - 25°C

(68 - 77°F.) Do not use if box has been

tampered with, or if the safety seal of the

bottle is broken.

Inactive ingredients:Ethanol 20% USP,

Purified Water.

QUESTIONS

Manufactured by: OHM pharma, Inc, USA.

Distributed by: Privia Naturals, LLC.

9169 W State St #196

Garden City, ID 83714

www.privianaturals.com

Info@privianaturals.com Product of USA.

PACKAGE LABEL

NDC 66343-101-60

RUBIMED

Emvita 14

Homeopathic Medicine For

General Well-being:

Feeling Hurt

2.0 fl oz. 59mL 20% Ethanol

PURPOSE

Homeopathic Medicine For

General Well-being:

Feeling Hurt